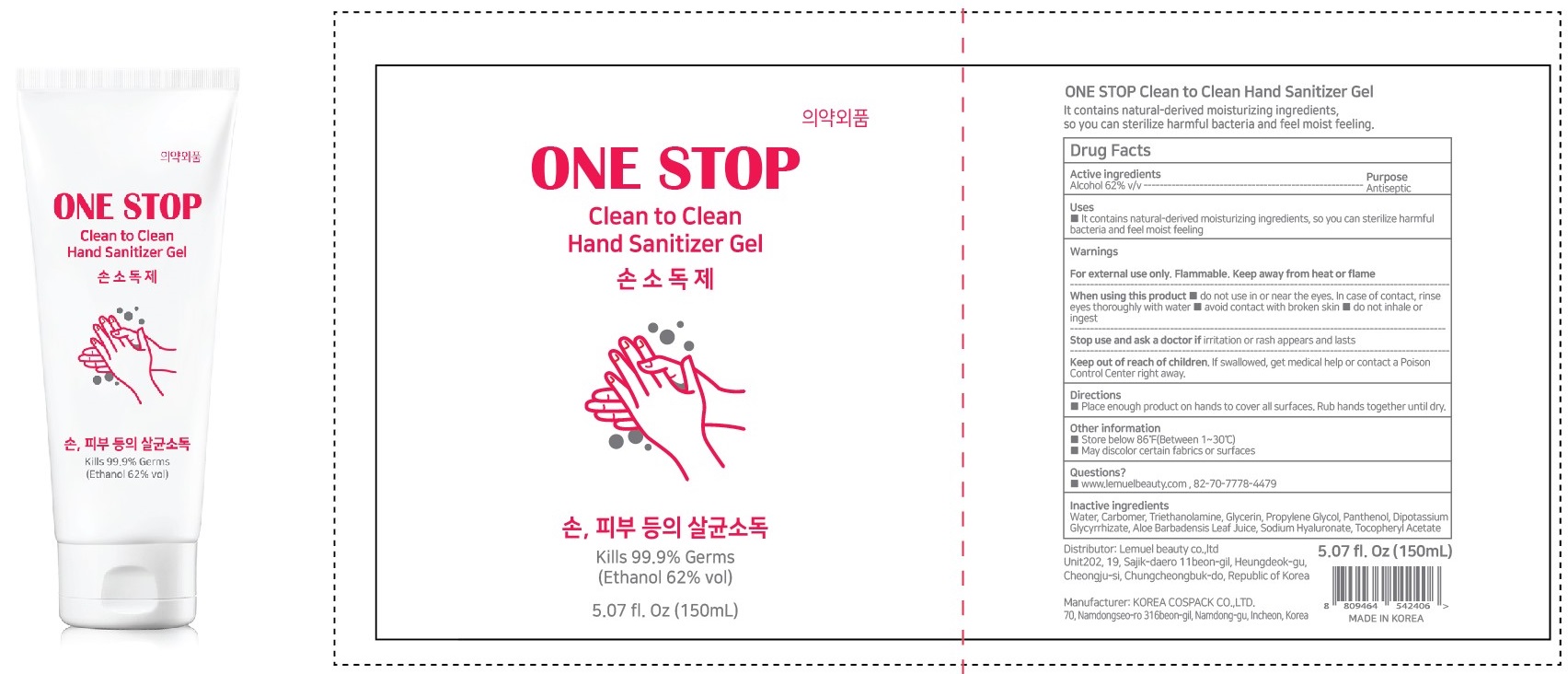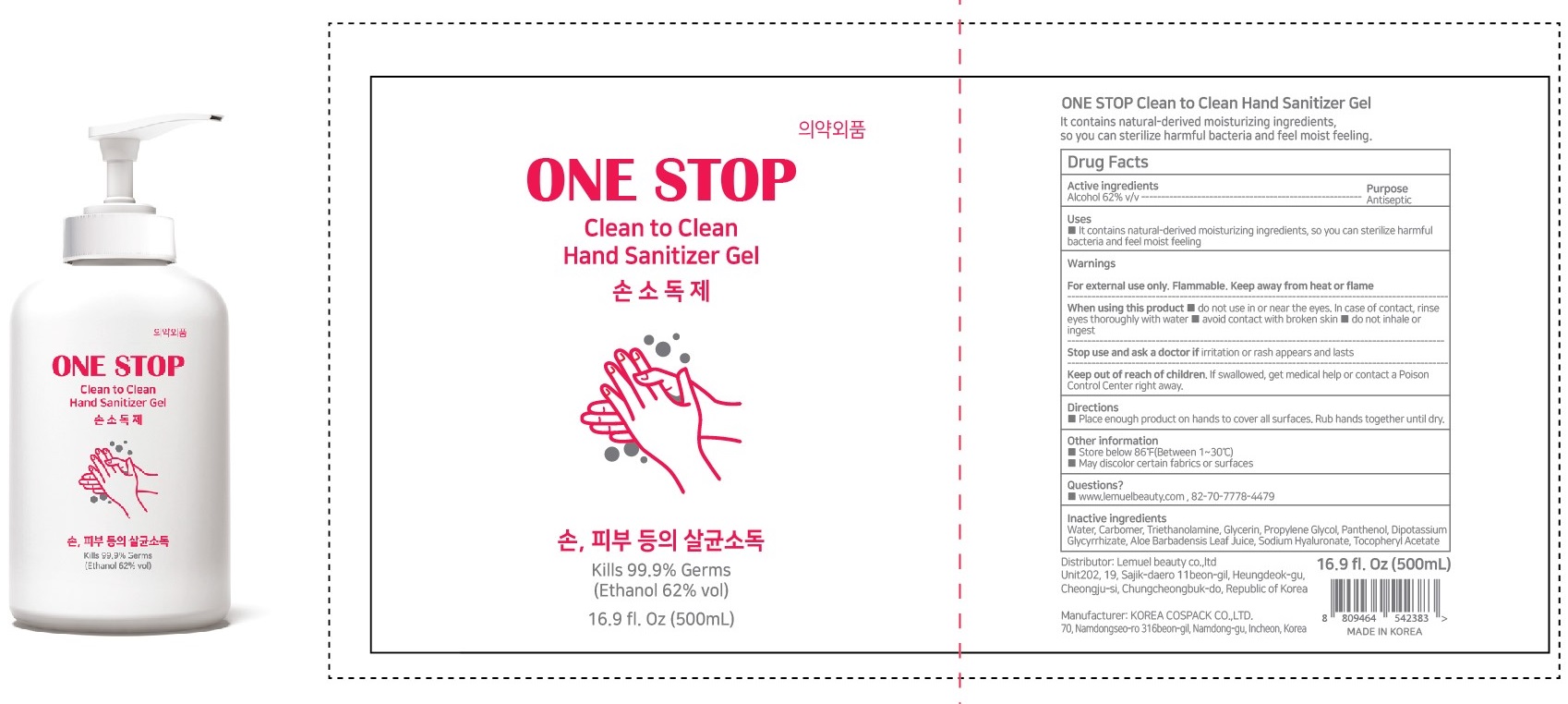 DRUG LABEL: ONE STOP Clean to Clean Hand Sanitizer
NDC: 77559-010 | Form: GEL
Manufacturer: LemuelBeauty Co.,Ltd
Category: otc | Type: HUMAN OTC DRUG LABEL
Date: 20200513

ACTIVE INGREDIENTS: ALCOHOL 62 mL/100 mL
INACTIVE INGREDIENTS: WATER; CARBOMER HOMOPOLYMER, UNSPECIFIED TYPE; TROLAMINE; Glycerin; Propylene Glycol; Panthenol; GLYCYRRHIZINATE DIPOTASSIUM; ALOE VERA LEAF; HYALURONATE SODIUM; .ALPHA.-TOCOPHEROL ACETATE

ACTIVE INGREDIENT

Alcohol 62% v/v

INACTIVE INGREDIENTS

Water, Carbomer, Triethanolamine, Glycerin, Propylene Glycol, Panthenol, Dipotassium Glycyrrhizate, Aloe Barbadensis Leaf Juice, Sodium Hyaluronate, Tocopheryl Acetate

PURPOSE

Antiseptic

WARNINGS

For external use only. Flammable. Keep away from heat or flame
--------------------------------------------------------------------------------------------------------
When using this product ■ do not use in or near the eyes. In case of contact, rinse eyes thoroughly with water ■ avoid contact with broken skin ■ do not inhale or ingest
--------------------------------------------------------------------------------------------------------
Stop use and ask a doctor if irritation or rash appears and lasts

KEEP OUT OF REACH OF CHILDREN

If swallowed, get medical help or contact a Poison Control Center right away.

Uses

■ It contains natural-derived moisturizing ingredients, so you can sterilize harmful bacteria and feel moist feeling

Directions

■ Place enough product on hands to cover all surfaces. Rub hands together until dry.

Other information

■ Store below 86℉(Between 1~30℃)
■ May discolor certain fabrics or surfaces

Questions?

■ www.lemuelbeauty.com , 82-70-7778-4479